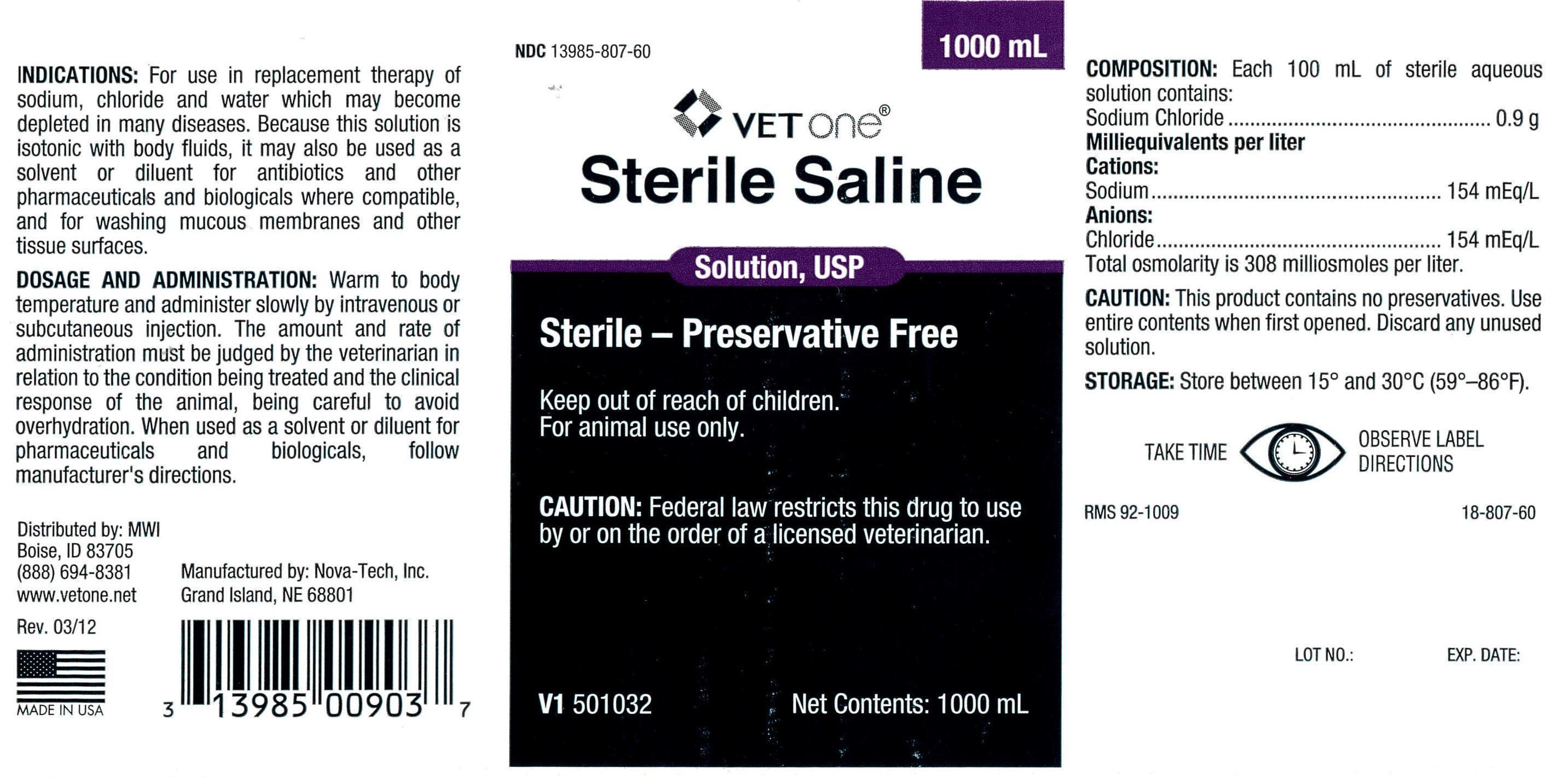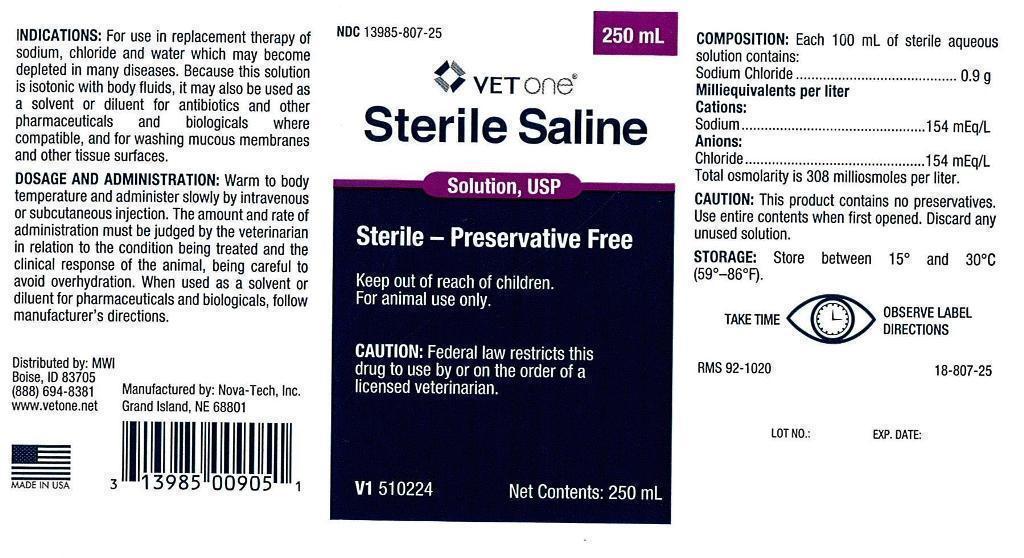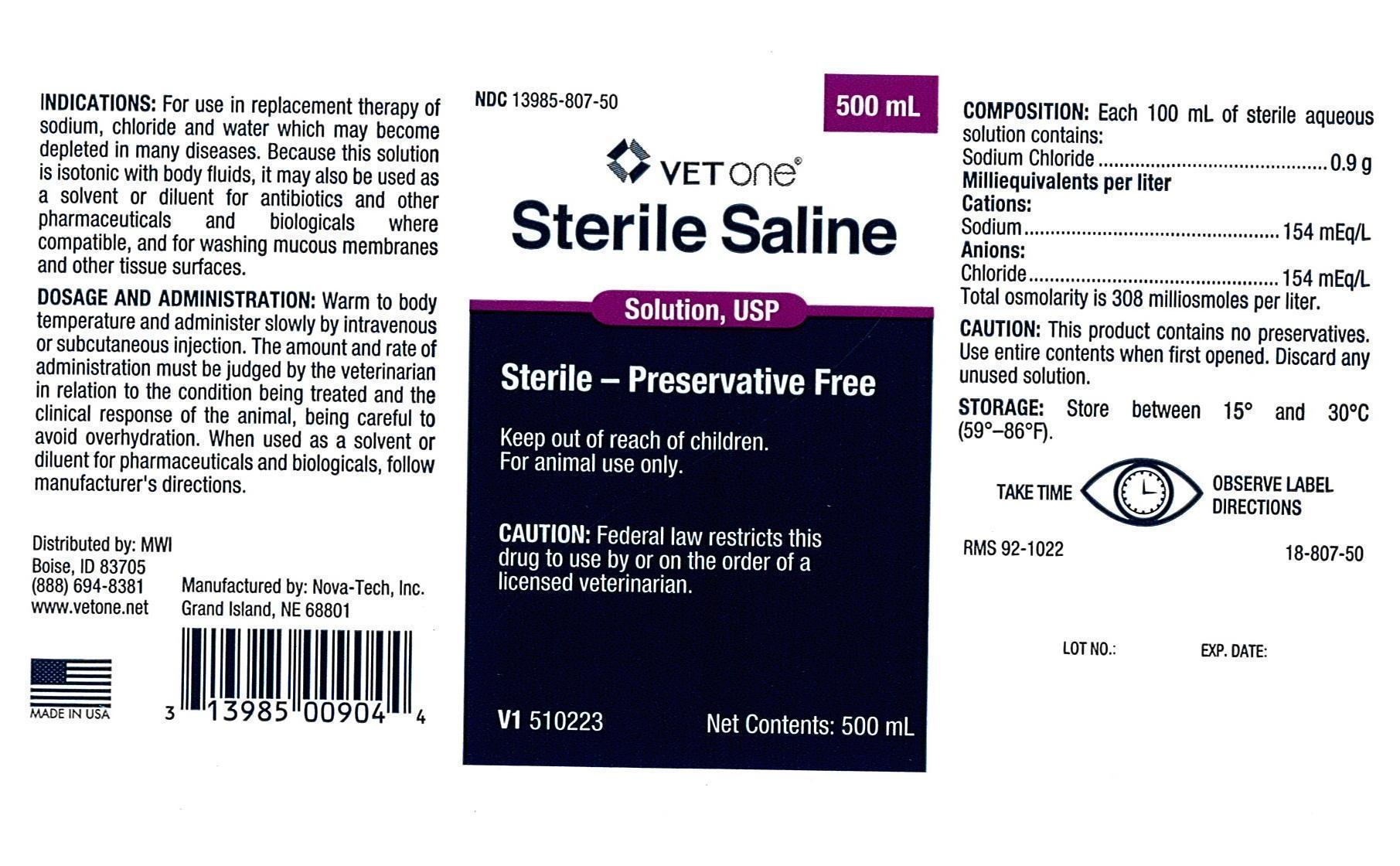 DRUG LABEL: Sterile Saline
NDC: 13985-807 | Form: INJECTION, SOLUTION
Manufacturer: MWI (VetOne)
Category: animal | Type: PRESCRIPTION ANIMAL DRUG LABEL
Date: 20151019

ACTIVE INGREDIENTS: Sodium Chloride 0.9 g/100 mL

Sterile Saline

INDICATIONS:

For use in replacement therapy of sodium, chloride and water which may become depleted in many diseases. Because this solution is isotonic with body fluids, it may also be used as a solvent or diluent for antibiotics and other pharmaceuticals and biologicals where compatible, and for washing mucous membranes and other tissue surfaces.

DOSAGE AND ADMINISTRATION:

Warm to body temperature and administer slowly by intravenous or subcutaneous injection. The amount and rate of administration must be judged by the veterinarian in relation to the condition being treated and the clinical response of the animal, being careful to avoid overhydration. When used as a solvent or diluent for pharmaceuticals and biologicals, follow manufacturer's directions.

Keep out of reach of children.

For animal use only.

CAUTION:

Federal law restricts this drug to use by or on the order of a licensed veterinarian.

COMPOSITION:

Each 100 mL of sterile aqueous solution contains:

Sodium Chloride ..................................0.9 g

Milliequivalents per liter

Cations:

Sodium .............................................154 mEq/L

Anions:

Chloride.............................................154 mEq/L

Total osmolarity is 308 milliosmoles per liter.

CAUTION:

This product contains no preservatives. Use entire contents when first opened. Discard any unused solution.

STORAGE:

Store between 15 degrees and 30 degrees C (59 degrees - 86 degrees F).

PRECAUTIONS

TAKE TIME OBSERVE LABEL DIRECTIONS